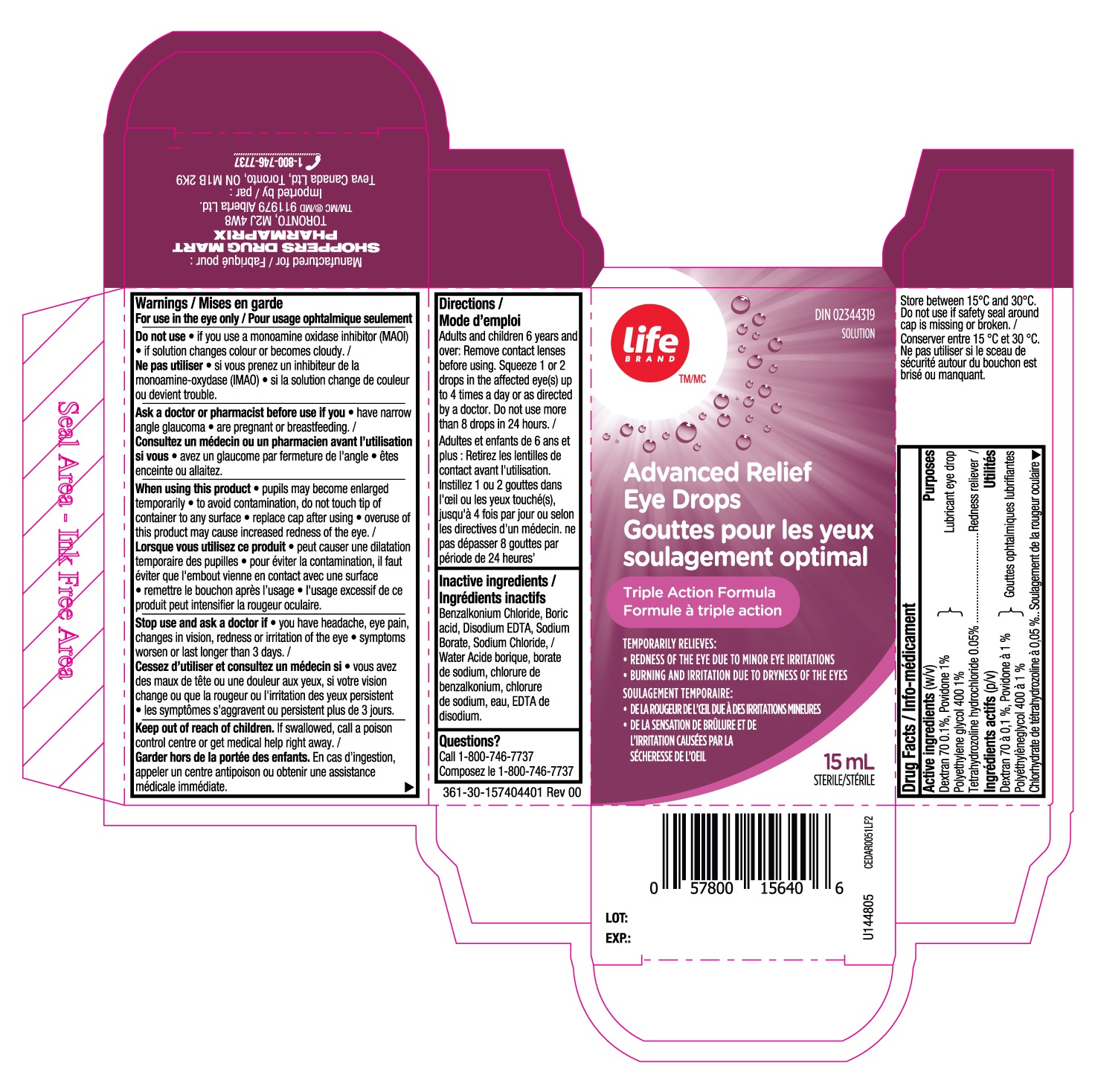 DRUG LABEL: Life Advanced Relief Eye Drops
NDC: 55651-004 | Form: SOLUTION/ DROPS
Manufacturer: K.C. Pharmaceuticals, Inc.
Category: otc | Type: HUMAN OTC DRUG LABEL
Date: 20251231

ACTIVE INGREDIENTS: DEXTRAN 70 0.1 g/100 mL; POLYETHYLENE GLYCOL 400 1 g/100 mL; POVIDONE 1 g/100 mL; TETRAHYDROZOLINE HYDROCHLORIDE 0.05 g/100 mL
INACTIVE INGREDIENTS: BENZALKONIUM CHLORIDE; BORIC ACID; EDETATE DISODIUM; WATER; SODIUM BORATE; SODIUM CHLORIDE

Life Advanced Relief Eye Drops (MFR - EXPORT to CANADA)